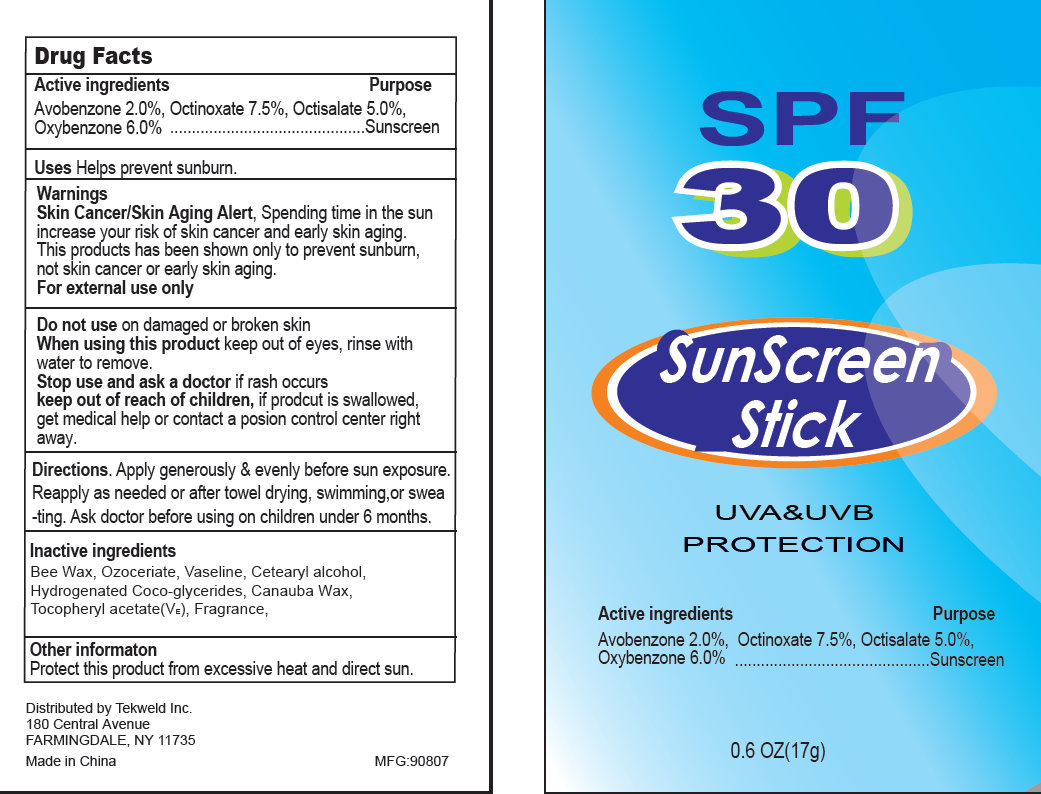 DRUG LABEL: SunScreen SPF 30
NDC: 31190-700 | Form: STICK
Manufacturer: Shanghai Kejing Cleaning Products Co., Ltd.
Category: otc | Type: HUMAN OTC DRUG LABEL
Date: 20110901

ACTIVE INGREDIENTS: AVOBENZONE 2.0 g/100 g; OCTINOXATE 7.5 g/100 g; OCTISALATE 5.0 g/100 g; OXYBENZONE 6.0 g/100 g
INACTIVE INGREDIENTS: CERESIN; PETROLATUM; CETOSTEARYL ALCOHOL ; COCO-GLYCERIDES; ALPHA-TOCOPHEROL ACETATE; YELLOW WAX; CARNAUBA WAX

SunScreen Stick SPF 30

Active Ingredient

Avobenzone 2.0 percent, Octinoxate 7.5 percent, Octisalate 5.0 percent

Oxybenzone 6.0 percent...............................................................Sunscreen

PURPOSE

Uses Helps prevent sunburn

Warnings

Skin Cancer/Skin Aging Alert, Spending time in the sun

increase your risk of skin cancer and early skin aging.

This products has been shown only to prevent sunburn only to prevent sunburn,

not skin cancer or early skin aging.

For external use only

Do not use on damaged or broken skin

When using this product keep out of eyes, rinse with

water to remove.

Stop use and ask a doctor if rash occurs

Keep out of reach of children, if product is swallowed,

get medical help or contact a poison control center right

away.

DOSAGE AND ADMINISTRATION

Directions. Apply generously and evenly before sun exposure.

Reapply as needed or after towel drying, swimming, or swea

-ting. Ask doctor before using on children under 6 months.

Inactive Ingredients

Bee wax, Ozoceriate, Vaseline, Cetearyl Alcohol,
Hydrogenated Coco-glycerides, Carnauba Wax,
Tocopheryl acetate (VE), Fragrance.

Other information

Protect this product from excessive heat and direct sun.

DESCRIPTION

Distributed by Tekweld Inc.

180 Central Avenue

FARMINGDALE, NY 11735

Made in China MFG:90807

PACKAGE LABEL

SPF

30

SunScreen

Stick

UVA and UVB

PROTECTION

Active Ingredients

Avobenzone 2.0 percent, Octinoxate 7.5 percent, Octisalate 5.0 percent
Oxybenzone 6.0 percent............................................................... Sunscreen

0.6 OZ(17g)